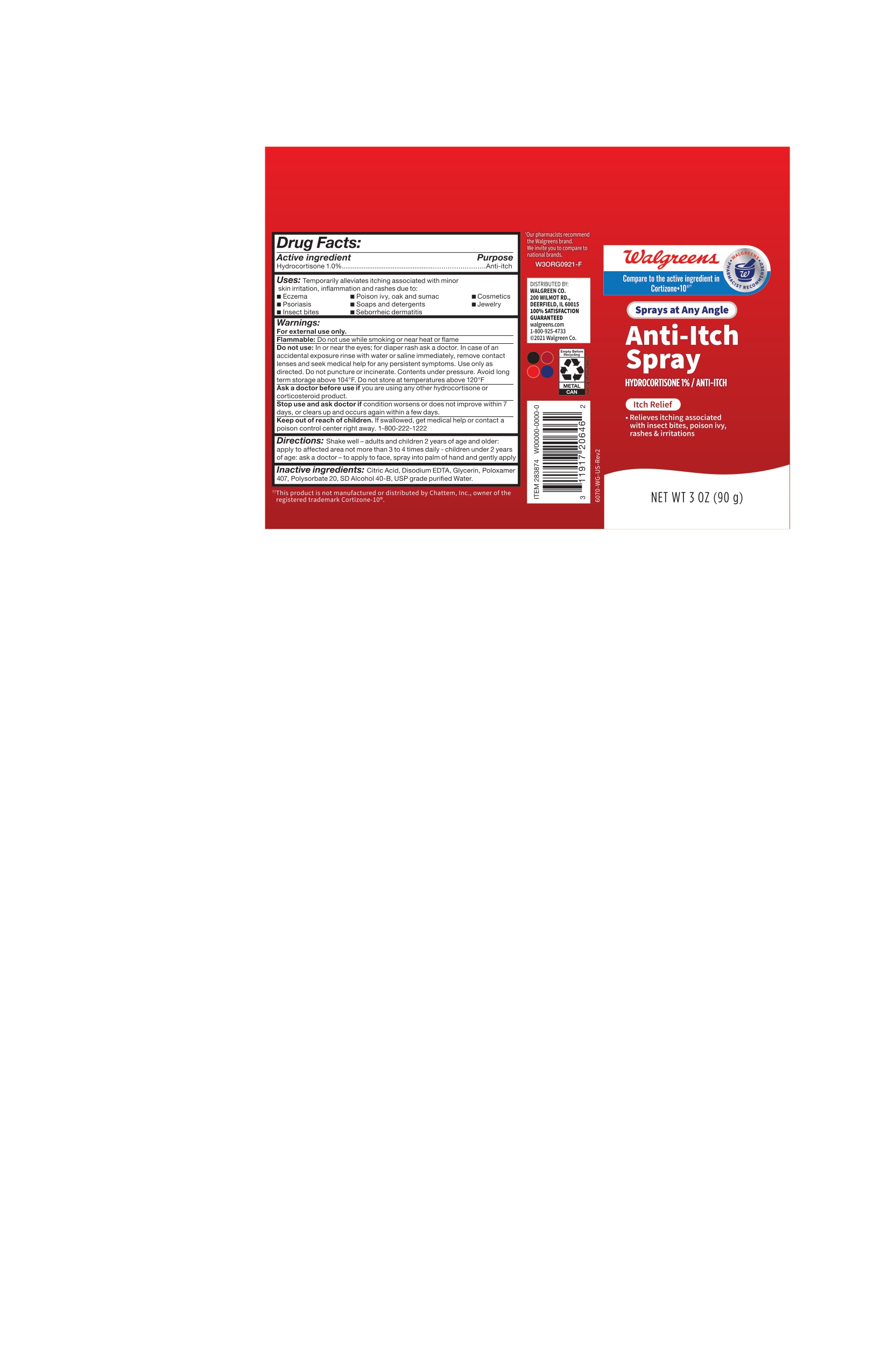 DRUG LABEL: Anti Itch
NDC: 0363-9801 | Form: SPRAY
Manufacturer: Walgreens
Category: otc | Type: HUMAN OTC DRUG LABEL
Date: 20250310

ACTIVE INGREDIENTS: HYDROCORTISONE 1 g/100 g
INACTIVE INGREDIENTS: EDETATE DISODIUM; POLYSORBATE 20; GLYCERIN; ALCOHOL; WATER; ANHYDROUS CITRIC ACID; POLOXAMER 407

DRUG FACTS - Active Ingredient

Hydrocortisone 1.0%

Purpose

Anti-Itch

Uses

Temporarily alleviates itching associated with minor skin irritation, inflammation and rashes due to:

- Eczema
- Poison ivy, oak and sumac
- Cosmetics
- Psoriasis
- Soaps and detergents
- Jewelry
- Insect bites
- Seborrheic dermatitis

Warnings

For external use only.

Flammable: Do not use while smoking or near heat or flame

Warnings: Do not use:

In or near the eyes; for diaper rash ask a doctor. In case of an accidental exposure rinse with water or saline immediately, remove contact lenses and seek medical help for any persistent symptoms. Use only as directed. Do not puncture or incinerate. Contents under pressure. Avoid long term storage above 104°F. Do not store at temperatures above 120°F.

Warnings: Ask a doctor before use if

you are using any other hydrocortisone or corticosteroid product.

Warnings: Stop use and ask doctor

if condition worsens or does not improve within 7 days, or clears up and occurs again within a few days.

Warnings: Keep out of reach of children

If swallowed, get medical help or contact a poison control center right away.

Directions:

Shake well

Adults and Children 2 years of age and older: apply to affected area not more than 3 to 4 times daily.

Children under 2 years of age: ask a doctor – to apply to face, spray into palm of hand and gently apply.

Inactive Ingredients:

Citric Acid, Disodium EDTA, Glycerin, Poloxamer 407, Polysorbate 20, SD Alcohol 40-B, USP grade purified Water.